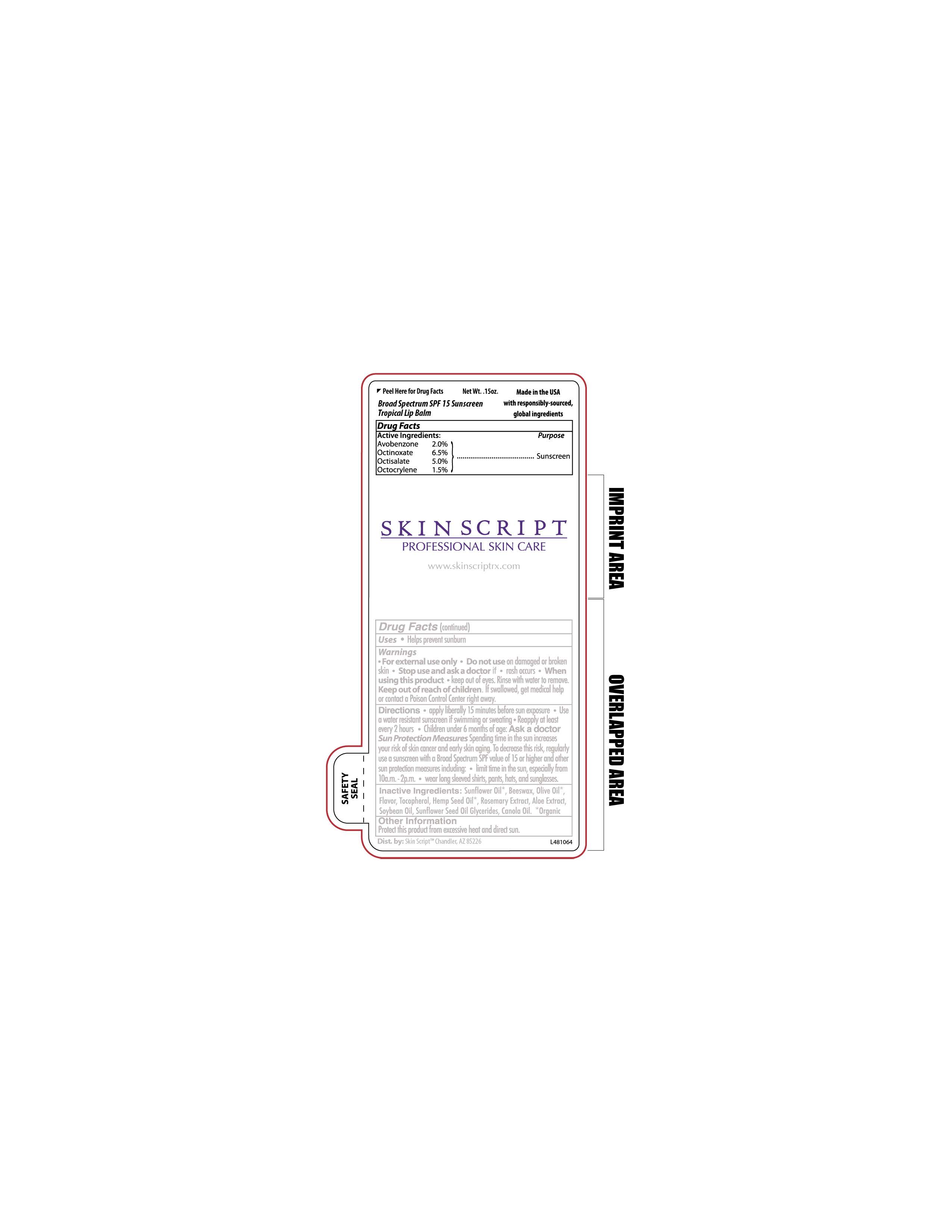 DRUG LABEL: Lip Balm SPF 15
NDC: 83657-600 | Form: LIPSTICK
Manufacturer: Skin Script, LLC
Category: otc | Type: HUMAN OTC DRUG LABEL
Date: 20240828

ACTIVE INGREDIENTS: OCTINOXATE 0.0065 g/1 g; OCTISALATE 0.005 g/1 g; OCTOCRYLENE 0.0015 g/1 g; AVOBENZONE 0.002 g/1 g
INACTIVE INGREDIENTS: SUNFLOWER OIL; CANNABIS SATIVA SEED OIL; ROSEMARY OIL; SOYBEAN OIL; SUNFLOWER OIL MONO/DIGLYCERIDES; CANOLA OIL; TOCOPHEROL; ALOE; OLIVE OIL

Active Ingredients:

Avobenzone 2.0%

Octinoxate 6.5%

Octisalate 5.0%

Octocrylene 1.5%

Purpose:

Sunscreen

Uses

- Helps prevent sunburn

QUESTIONS

Dist. by: Skin ScriptTM Chandler, AZ 85226

Warnings

- For External Use Only
- Do not use on damaged or broken skin
- Stop and ask a doctor if
  - rash occurs
- When using this product
- keep out of eyes. Rinse with water to remove.

Keep out of reach of children.

If swallowed, get medical help or contact a Poison Control Center right away.

Directions

- apply liberally 15 minutes before sun exposure
- Use a water resistant sunscreen if swimming or sweating
- Reapply at least every 2 hours
- Children under 6 months of age: Ask a doctor

Sun Protection Measures

Spending time in the sun increases your risk of skin cancer and early skin aging. To decrease this risk, regularly use a sunscreen with Broad Spectrum SPF value of 15 or higher and other sun protection measures including:

- limit time in the sun, especially from 10a.m. - 2p.m.
- wear long sleeved shirts, pants, hats, and sunglasses.

Inactive Ingredients:

Sunflower Oil*, Beeswax, Olive Oil*, Flavor, Tocopherol, Hemp Seed Oil*, Rosemary Extract, Aloe Extract, Soybean Oil, Sunflower Seed Oil Glycerides, Canola Oil. *Organic

Other Information

Protect this product from excessive heat and direct sun.

RECENT MAJOR CHANGES

Corrected Indications and usage section